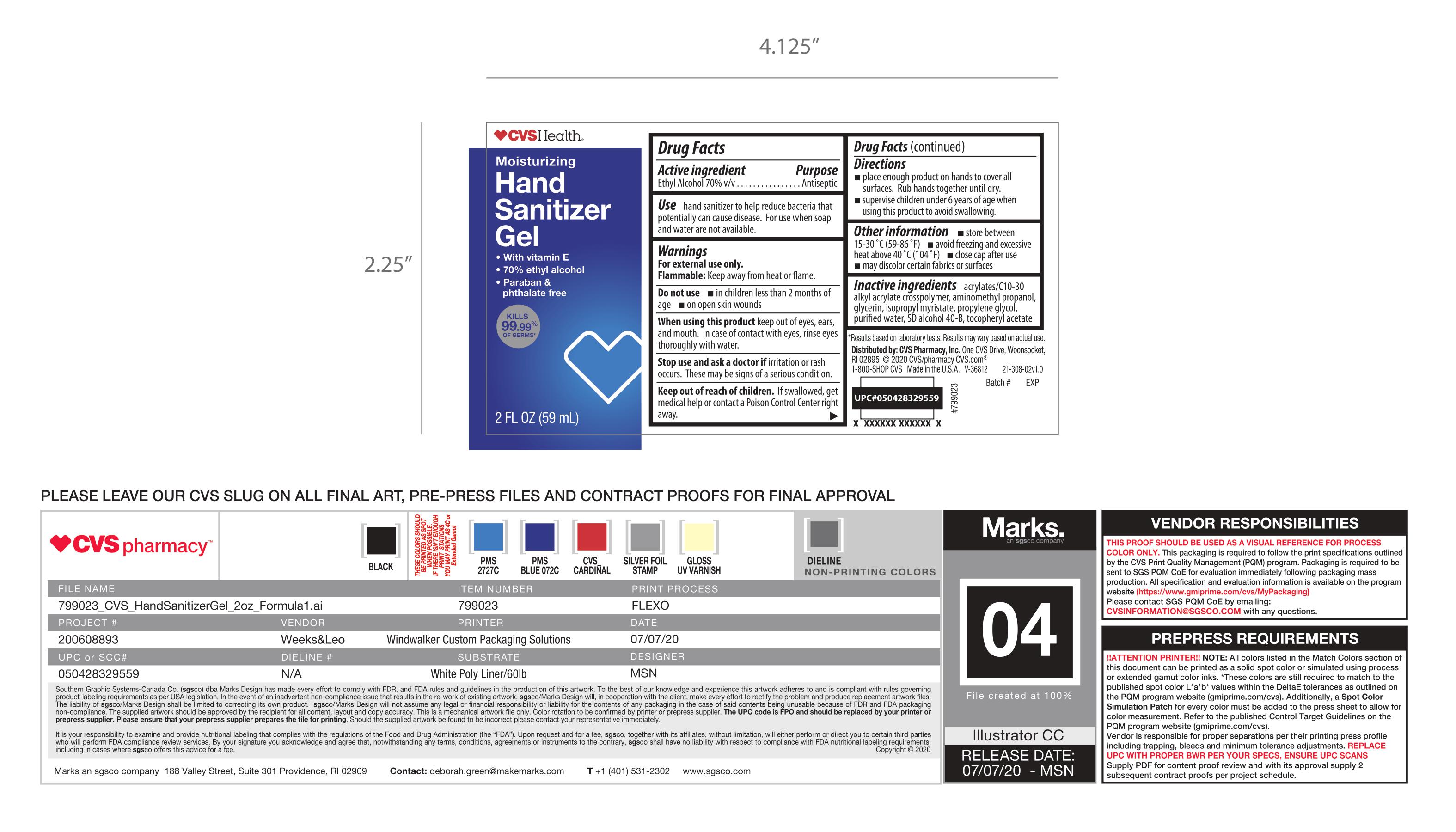 DRUG LABEL: CVS Hand Sanitizer
NDC: 69842-760 | Form: GEL
Manufacturer: CVS
Category: otc | Type: HUMAN OTC DRUG LABEL
Date: 20241210

ACTIVE INGREDIENTS: ALCOHOL 70 mL/100 mL
INACTIVE INGREDIENTS: .ALPHA.-TOCOPHEROL ACETATE; PROPYLENE GLYCOL; GLYCERIN; WATER; BUTYL ACRYLATE/METHYL METHACRYLATE/METHACRYLIC ACID COPOLYMER (18000 MW); ISOPROPYL MYRISTATE; AMINOMETHYLPROPANOL

CVS Hand Sanitizer

Active Ingredients

Alcohol 70% v/v..................................................................Antiseptic

Purpose

Antiseptic

Uses

hand sanitizer to help reduce bacteria that potentially can cause disease. For use when soap and water are not available

Warnings

For external use only

Do not use

in children less than 2 months of age.

on open skin wounds

When using this product

keep out of eyes, ears, and mouth. In case of contact with eyes, rinse eyes thoroughly with water.

Stop use and ask a doctor

Irritation or rash occurs. These may be signs of a serious condition

Keep out of reach of children

If swallowed, get medical help or contact a Poison Control Center right away

Directions

Place enough product on hands to cover all surfaces. Rub hands together until dry.
Supervise children under 6 years of age when using this product to avoid swallowing

Other Information

Store between 15–30 °C (59–86 °F)
Avoid freezing and excessive heat above 40 °C (104 °F)
Close cap after use
May discolor certain fabrics or surfaces

Inactive Ingredients

acrylates/C10–30 alkyl acrylate crosspolymer, aminomethyl propanol, glycerin, isopropyl myristate,propylene glycol, purified water, SD alcohol 40-B, tocopheryl acetate

PACKAGE LABEL

CVS Health

Moisturizing Hand Sanitizer Gel

With Vitamin E

70% ethyl alcohol

Paraban & phthalate free